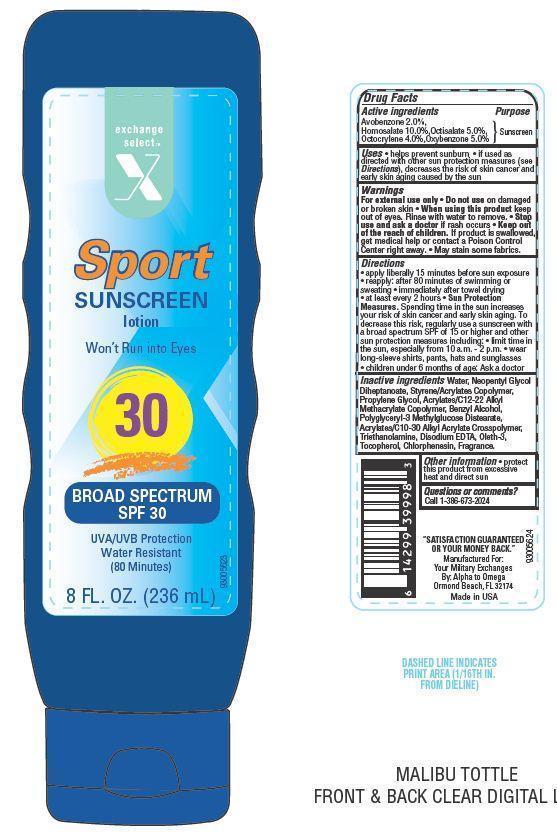 DRUG LABEL: EXSEL SPORT
NDC: 55301-015 | Form: LOTION
Manufacturer: ARMY AND AIR FORCE EXCHANGE SERVICE
Category: otc | Type: HUMAN OTC DRUG LABEL
Date: 20130806

ACTIVE INGREDIENTS: AVOBENZONE 2 g/100 g; HOMOSALATE 10 g/100 g; OCTISALATE 5 g/100 g; OCTOCRYLENE 4 g/100 g; OXYBENZONE 5 g/100 g
INACTIVE INGREDIENTS: WATER; NEOPENTYL GLYCOL DIHEPTANOATE; PROPYLENE GLYCOL; BENZYL ALCOHOL; CARBOMER INTERPOLYMER TYPE A (55000 CPS); TROLAMINE; EDETATE DISODIUM; TOCOPHEROL; CHLORPHENESIN; OLETH-3

Drug Facts

Active ingredients

Avobenzone 2.0%

Homosalate 10.0%

Octisalate 5.0%

Octocrylene 4.0%

Oxybenzone 5.0%

Purpose

Sunscreen

Uses

- Helps prevent sunburn
- If used as directed with other sun protection measures (see Directions), decrease the risk of skin cancer and early skin aging caused by the sun.

Warnings

For external use only. Do not use on damaged or broken skin.

When using this product

Keep out of eyes. Rinse with water to remove.

Stop use and ask a doctor

if rash occurs

Keep out of reach of children

If swallowed, get medical help or contact a Poison Control Center right away. May stain some fabrics.

Directions

- apply liberally 15 minutes before sun exposure
- reapply
- after 80 minutes of swimming or sweating
- immediately after towel drying
- at least every 2 hours
- Sun Protection Measures: Spending time in the sun increases your risk of skin cancer and early skin aging. To decrease this risk, regularly use a sunscreen with a broad spectrum SPF of 15 or higher and other sun protection measures including:
- limit time in the sun, especially from 10 a.m. - 2 p.m.
- wear long-sleeve shirts, pants, hats and sunglasses
- children under 6 months of age: Ask a doctor

Inactive ingredients

Water, Neopentyl Glycol Diheptanoate, Styrene/Acrylates Copolymer, Propylene Glycol, Acrylates/C12-22 Alkyl Methacrylate Copolymer, Benzyl Alcohol, Polyglyceryl-3 Methylglucose Distearate, Acrylates/C10-30 Alkyl Acrylate Crosspolymer, Triethanolamine, Disodium EDTA, Tocopherol, Oleth-3, Chlorphenesin, Fragrance.

Other Information

- protect this product from excessive heat and direct sun

Principal Display Panel

exchange select

X

Sport

SUNSCREEN

lotion

Won't Run into Eyes

30

Broad Spectrum SPF 30

UVA/UVB Protection

Water Resistant

(80 Minutes)

8 FL. OZ. (236 mL)

Questions or comments?

Call 1-386-673-2024